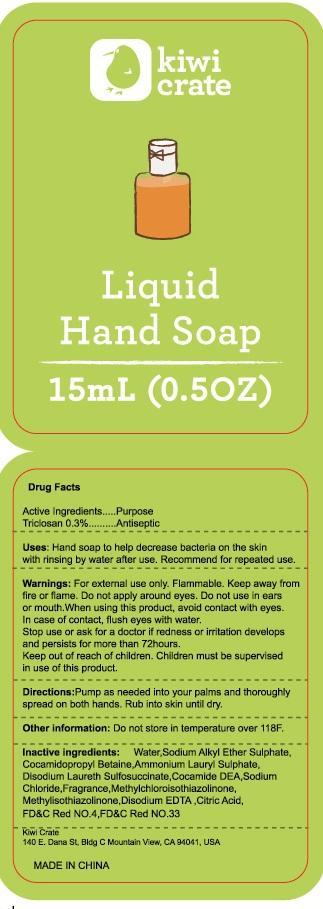 DRUG LABEL: kiwi crate Liquid Hand
NDC: 69034-001 | Form: SOAP
Manufacturer: Kiwi Crate
Category: otc | Type: HUMAN OTC DRUG LABEL
Date: 20140606

ACTIVE INGREDIENTS: TRICLOSAN 0.3 g/100 mL
INACTIVE INGREDIENTS: WATER; SODIUM C12-15 PARETH-3 SULFATE; COCAMIDOPROPYL BETAINE; AMMONIUM LAURYL SULFATE; DISODIUM LAURETH SULFOSUCCINATE; COCO DIETHANOLAMIDE; SODIUM CHLORIDE; METHYLCHLOROISOTHIAZOLINONE; METHYLISOTHIAZOLINONE; EDETATE DISODIUM; CITRIC ACID MONOHYDRATE; FD&C RED NO. 4; D&C RED NO. 33

Active ingredient:

Triclosan 0.3%

Purpose
Antiseptic

INDICATIONS AND USAGE

Uses: Hand soap to help decrease bacteria on the skin with rinsing by water after use. Recommended for repeated use.

Warnings: For external use only.

Flammable. Keep away from fire or flame.

Do not apply around eyes.

Do not use in ears or mouth.
When using this product, avoid contact with eyes. In case of contact, flush eyes with water.

Stop use or ask for a doctor if redness or irritation develops and persists for more than 72 hours.

Keep out of reach of children. Children must be supervised in use of this product.

DOSAGE AND ADMINISTRATION

Directions: Pump as needed into your palms and thoroughly spread on both hands. Rub into skin until dry.

Other information: Do not store in temperature over 118 F.

INACTIVE INGREDIENT

Inactive Ingredients: Water, Sodium Alkyl Ether Sulphate, Cocamidopropyl Betaine, Ammonium Lauryl Sulphate, Disodium Laureth Sulfosuccinate, Cocamide DEA, Sodium Chloride, Fragrance, Methylchloroisothiazolinone, Methylisothiazolinone, Disodium EDTA, Citric Acid, FD&C Red NO.4, FD&C Red NO.33